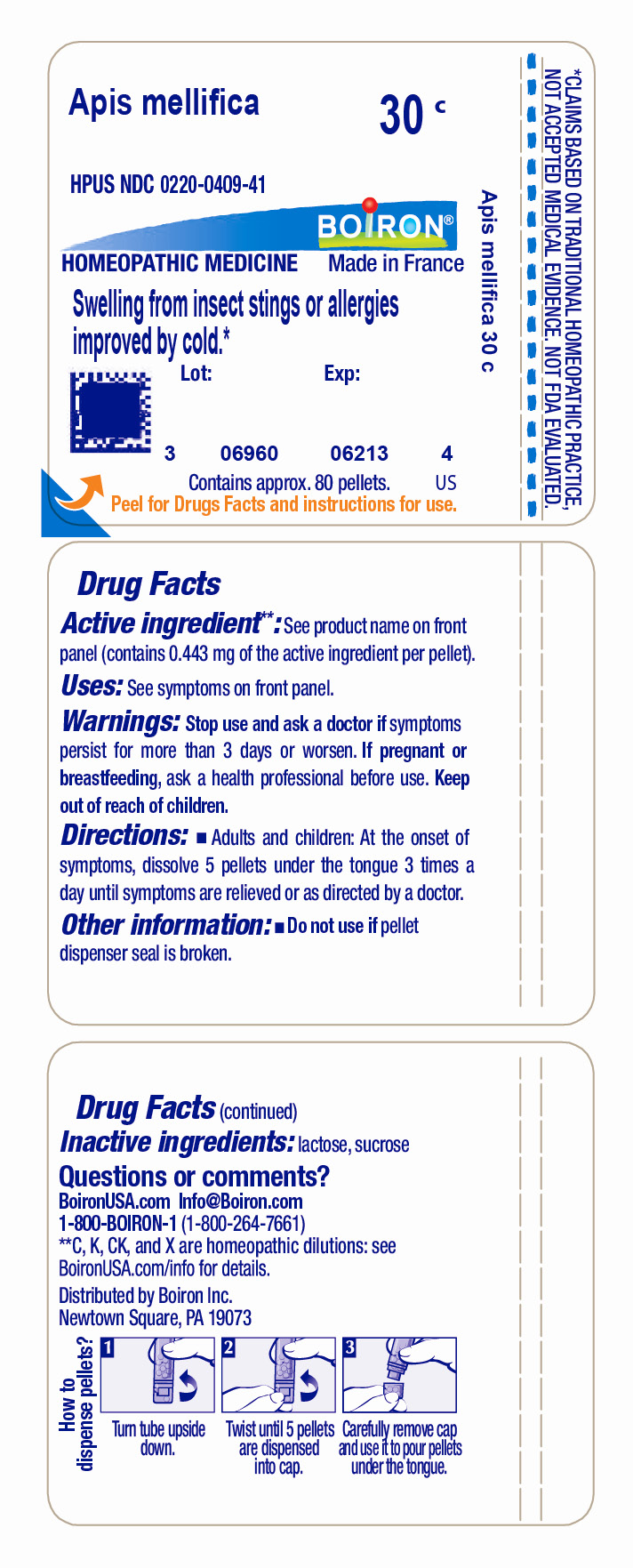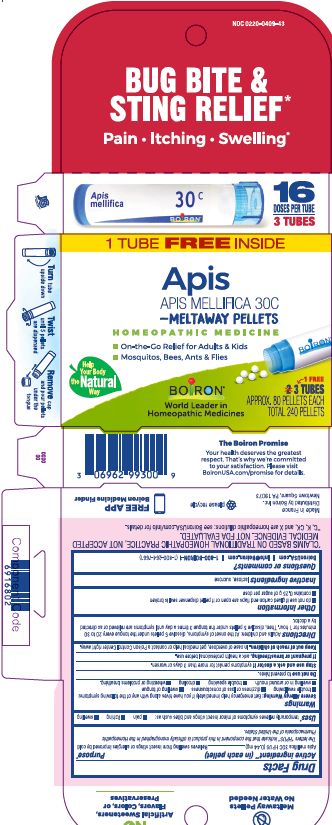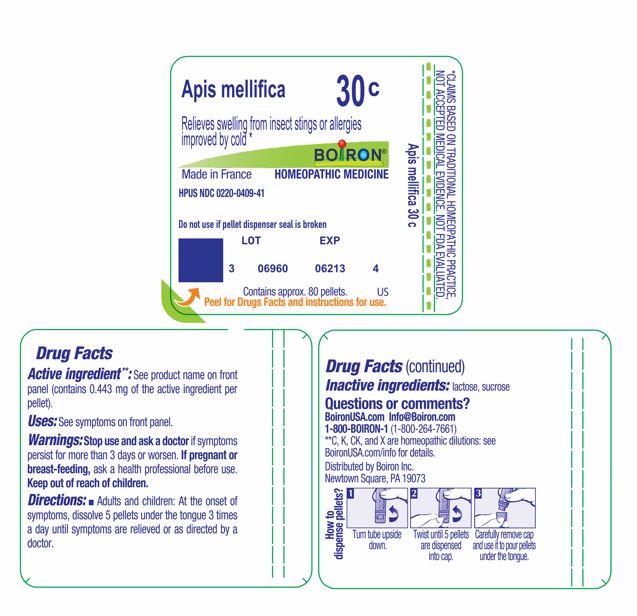 DRUG LABEL: Apis mellifica
NDC: 0220-0409 | Form: PELLET
Manufacturer: Boiron
Category: homeopathic | Type: HUMAN OTC DRUG LABEL
Date: 20241219

ACTIVE INGREDIENTS: APIS MELLIFERA 30 [hp_C]/30 [hp_C]
INACTIVE INGREDIENTS: LACTOSE, UNSPECIFIED FORM; SUCROSE

Apis mellifica 30C

Active ingredient** (in each pellet)

Apis mellifica 30C HPUS (0.44 mg)

The letters "HPUS" indicate that the component in this product is officially monographed in the Homeopathic Pharmacopoeia of the United States.

Purpose*

Relieves swelling from insect stings or allergies improved by cold

Uses*

Box- temporarily relieves symptoms of minor insect stings and bites such as:

- pain
- itching
- swelling

Tube- Relieves swelling from insect stings or allergies improved by cold *

WARNINGS

Severe Allergy Warning: Get emergency help immediately if you have hives along with any of the following symptoms:

- trouble swallowing
- dizziness or loss of consciousness
- swelling of tongue
- swelling in or around mouth
- trouble speaking
- drooling
- wheezing or problems breathing.

Do not use to prevent hives.

Stop use and ask a doctor if symptoms persist for more than 3 days or worsen.

PREGNANCY OR BREAST FEEDING

If pregnant or breastfeeding, ask a health professional before use.

Keep out of reach of children. In case of overdose, get medical help or contact a Poison Control Center right away.

DOSAGE AND ADMINISTRATION

Box - Adults and children: At the onset of symptoms, dissolve 5 pellets under the tongue every 20 to 30 minutes for 1 hour. Then, dissolve 5 pellets under the tongue 3 times a day until symptoms are relieved or as directed by a doctor.

Tube - Adults and children: At the onset of symptoms, dissolve 5 pellets under the tongue 3 times a day until symptoms are relieved or as directed by a doctor.

INACTIVE INGREDIENT

lactose, sucrose

QUESTIONS

1-800-BOIRON-1 (1-800-264-7661),
BoironUSA.com Info@boiron.com
Distributed by Boiron, Inc. Newtown Square, PA 19073

- do not use if glued carton end flaps are open or if pellet dispenser seal is broken
- contains 0.25 g of sugar per dose

Bug Bite & Sting Relief*

Pain Itching Swelling*

On-the-Go Relief for Adults & Kids

Turn tube upside down Twist until 5 pellets are dispensed Remove cap and pour pellets under the tongue

3 TUBES

APPROX. 80 PELLETS EACH

TOTAL 240 PELLETS

16 DOSES PER TUBE

Do not use if pellet dispenser seal is broken.
Contains approx 80 pellets.
How to dispense pellets? Turn tube upside down. Twist until 5 pellets are dispensed into cap. Carefully remove the cap and use it to pour pellets under the tongue.

*CLAIMS BASED ON TRADITIONAL HOMEOPATHIC PRACTICE NOT ACCEPTED MEDICAL EVIDENCE. NOT FDA EVALUATED.
*C,K,CK, and X are homeopathic dilutions: see BoironUSA.com/info for details.